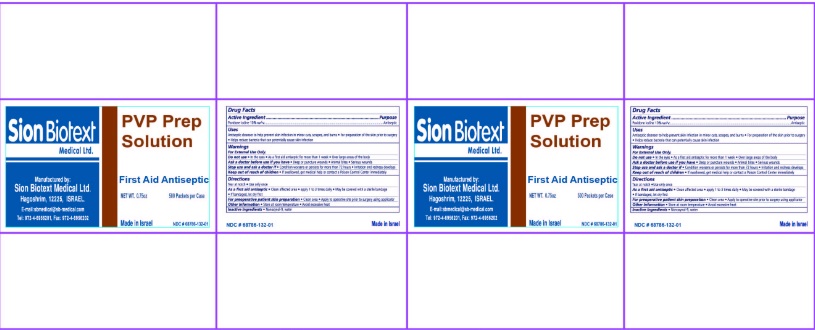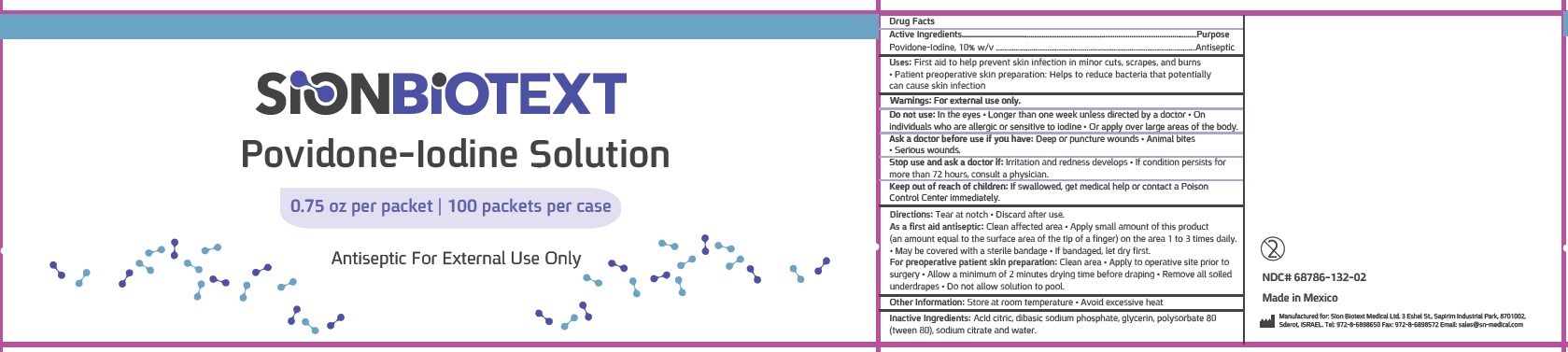 DRUG LABEL: Povidone Iodine Prep
NDC: 68786-132 | Form: SOLUTION
Manufacturer: Sion Biotext Medical Ltd
Category: otc | Type: HUMAN OTC DRUG LABEL
Date: 20250904

ACTIVE INGREDIENTS: POVIDONE-IODINE 1 g/100 mL
INACTIVE INGREDIENTS: SODIUM CITRATE; POLYSORBATE 80; GLYCERIN; SODIUM PHOSPHATE, DIBASIC, UNSPECIFIED FORM; CITRIC ACID; NONOXYNOL-9; WATER

Drug Facts

Active ingredient

Povidone Iodine 10% w/v

Purpose

Antiseptic

Uses

- Antiseptic cleanser to help prevent skin infection in minor cuts, scrapes, and burns
- For preparation of the skin prior to surgery
- Helps reduce bacteria that can potentially cause skin infection

Warnings:

For External Use Only.

Do not use

- In the eyes
- As a first aid antiseptic for more than 1 week
- Over large areas of the body

Ask a doctor before use if you have

- Deep or puncture wounds
- Animal bites
- Serious wounds

Stop use and ask a doctor if

- Condition worsens or persists for more than 72 hours
- Irritation and redness develops

Keep out of reach of children

- If swallowed, get medical help or contact a Poison Control Center immediately.

Directions:

- Tear at notch

- Use only once

As a first aid antiseptic

- Clean affected area
- apply 1 to 3 times daily
- May be covered with a sterile bandage
- If bandaged, let dry first.

For preoperative patient skin preparation

- Clean affected area
- Apply to operative site prior to surgery using applicator

Other information

- Store at room temperature
- Avoid excessive heat

Inactive Ingredients:

- Nonoxynol-9, water

Principal Display Panel

PVP Prep Solution

First Aid Antiseptic

NET WT. 0.75 oz

500 Packets per Case

Made in Israel

NDC 68786-132-01

100 Packets per case

NDC 68786-132-02